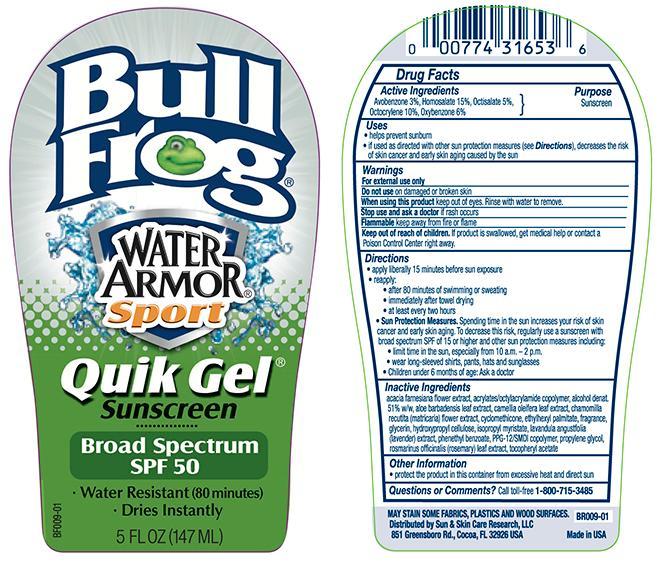 DRUG LABEL: Bull Frog Water Armor Sport Quik 50
NDC: 62802-653 | Form: GEL
Manufacturer: Sun & Skin Care Research, LLC
Category: otc | Type: HUMAN OTC DRUG LABEL
Date: 20140325

ACTIVE INGREDIENTS: HOMOSALATE 15 g/100 g; OCTISALATE 5 g/100 g; OXYBENZONE 6 g/100 g; OCTOCRYLENE 10 g/100 g; AVOBENZONE 3 g/100 g
INACTIVE INGREDIENTS: ALOE VERA LEAF; ALCOHOL; GLYCERIN; CYCLOMETHICONE; ETHYLHEXYL PALMITATE; CAMELLIA OLEIFERA LEAF; CHAMOMILE FLOWER OIL; ISOPROPYL MYRISTATE; LAVANDULA ANGUSTIFOLIA FLOWER; ROSMARINUS OFFICINALIS FLOWER; HYDROXYPROPYL CELLULOSE; PHENETHYL BENZOATE; PPG-12/SMDI COPOLYMER; PROPYLENE GLYCOL; .ALPHA.-TOCOPHEROL ACETATE

Drug Facts

Active Ingredients

Homosalate: 15%
Octisalate: 5%
Oxybenzone: 6%
Octocrylene: 10%
Avobenzone: 3%

Purpose

Sunscreen

Uses

- helps prevent sunburn
- If used as directed with other skin protection measures (see Directions), decreases the risk of skin cancer and early skin aging caused by the sun.

Warnings

For external use only. Do not use on damaged or broken skin. Stop use and ask a doctor if rash occurs. When using this product keep out of eyes. Rinse with water to remove. Keep out of the reach of children. If swallowed, get medical help or contact a Poison Control Center right away. Flammable Keep away from fire or flame.

Directions

- Apply liberally 15 minutes before sun exposure
- reapply after 80 minutes of swimming or sweating and immediately after towel drying
- at least every 2 hours
- Sun Protection Measures. Spending time in the sun increases your risk of skin cancer and early skin aging. To decrease this risk, regularly use a sunscreen with a Broad Spectrum SPF value of 15 or higher and other sun protection measures including limiting time in the sun, especially from 10a.m.-2p.m., wear long-sleeved shirts, pants hats and sunglasses.
- children under 6 months: Ask a doctor.

Other Information

- For use on skin only
- Avoid contact with fabric
- Protect this product from excessive heat and direct sun